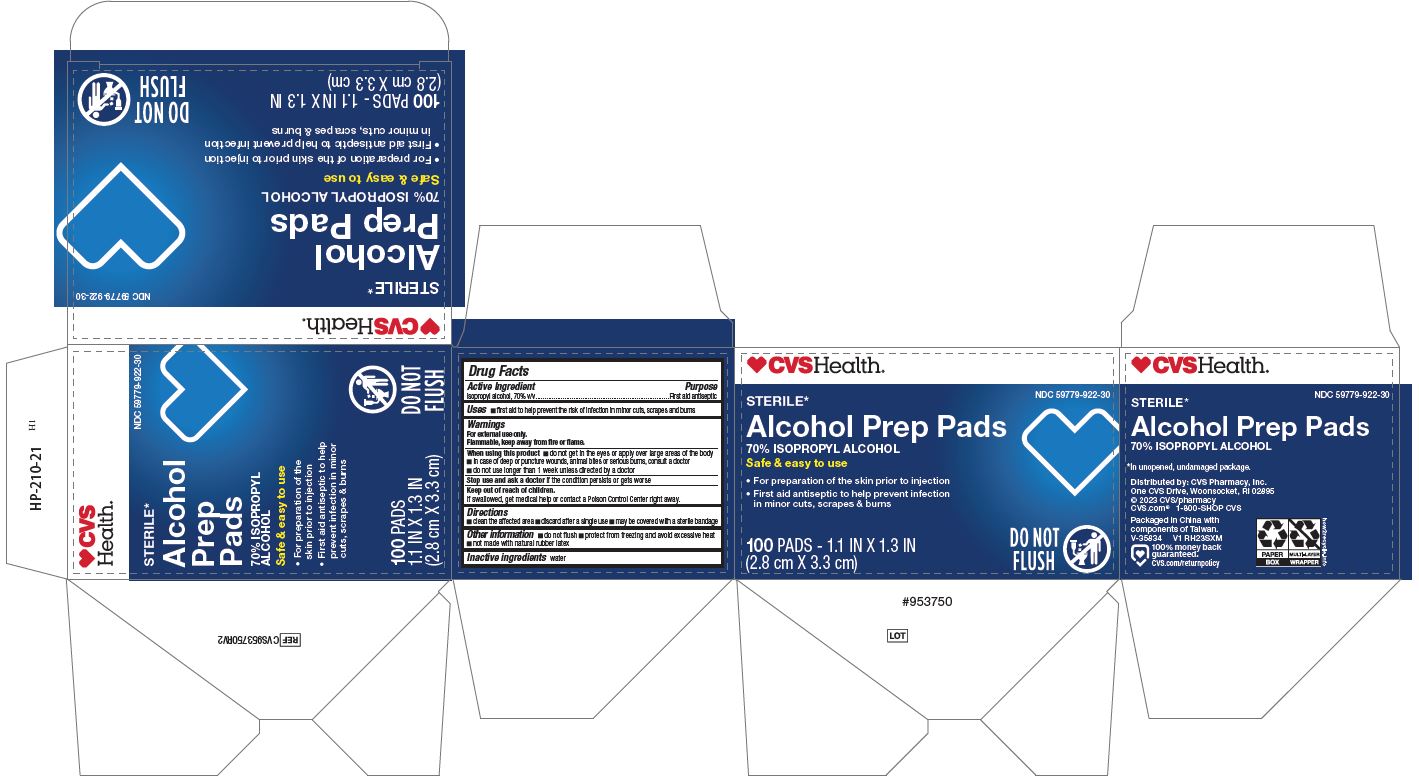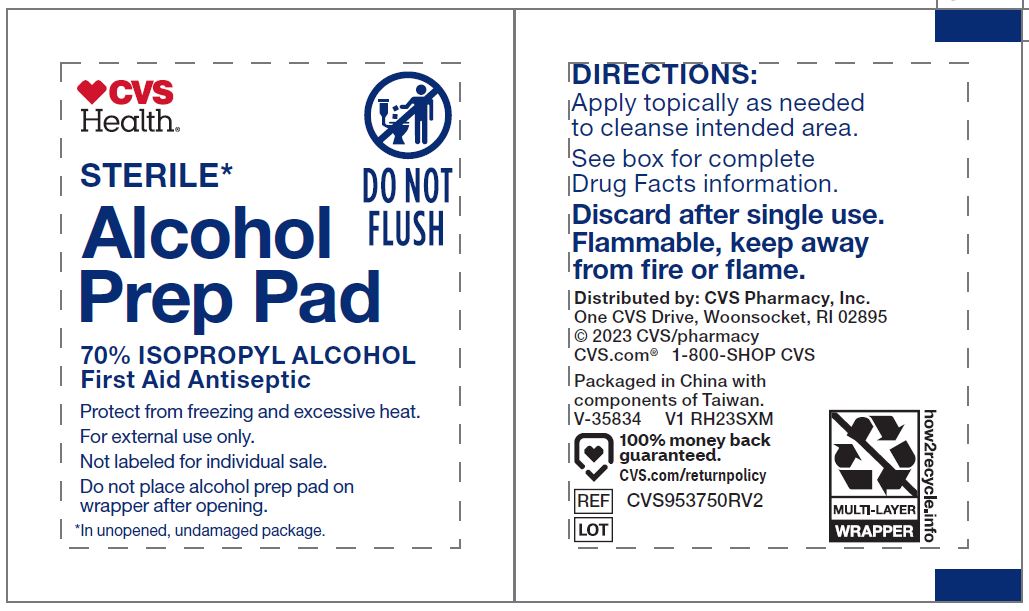 DRUG LABEL: CVS Alcohol Prep
NDC: 59779-922 | Form: SWAB
Manufacturer: CVS Pharmacy
Category: otc | Type: HUMAN OTC DRUG LABEL
Date: 20251020

ACTIVE INGREDIENTS: ISOPROPYL ALCOHOL 70 mL/100 mL
INACTIVE INGREDIENTS: WATER

59779-922 CVS IPA Swab

Active ingredient

Isopropyl alcohol 70% v/v

Purpose

First aid antiseptic

Uses

- first aid to help prevent the risk of infection in minor cuts, scrapes and burns

Warnings

For external use only.

Flammable, keep away from fire or flame.

When using this product

- do not get in the eyes or apply over large areas of the body
- in case of deep or puncture wounds, animal bites or serious burns, consult a doctor
- do not use longer than 1 week unless directed by a doctor

Stop use and ask a doctor if

- the condition persists or gets worse

Keep out of reach of children.

If swallowed, get medical help or contact a Poison Control Center right away.

Directions

- clean the affected area
- discard after a single use
- may be covered with a sterile bandage

Other information

- do not flush
- protect from freezing, avoid excessive heat
- not made with natural rubber latex

Inactive ingredients

water

Manufacturing Information

Distributed by: CVS Phamacy, Inc.

One CVS Drive, woonsocket, RI 02895 USA

Made in China

1-800-SHOP CVS

www.CVS.com

REF: CVS953750RV2

V1 RH23SXM